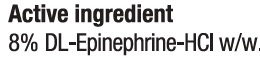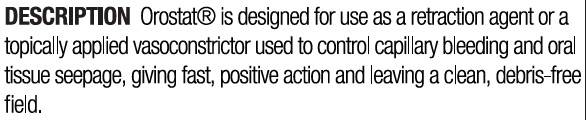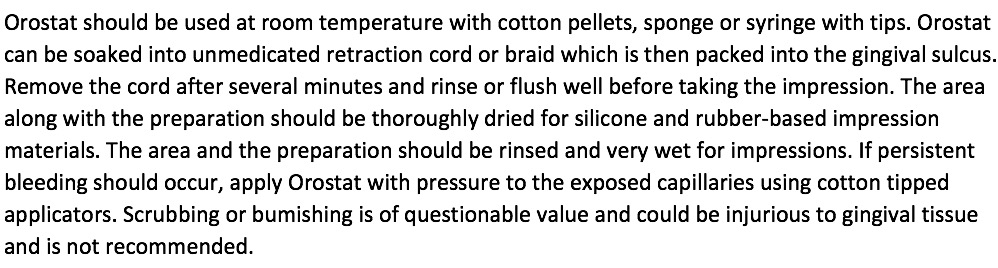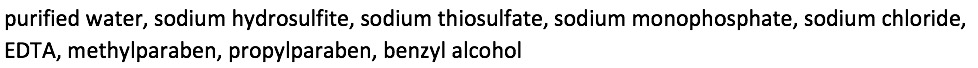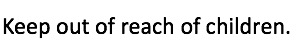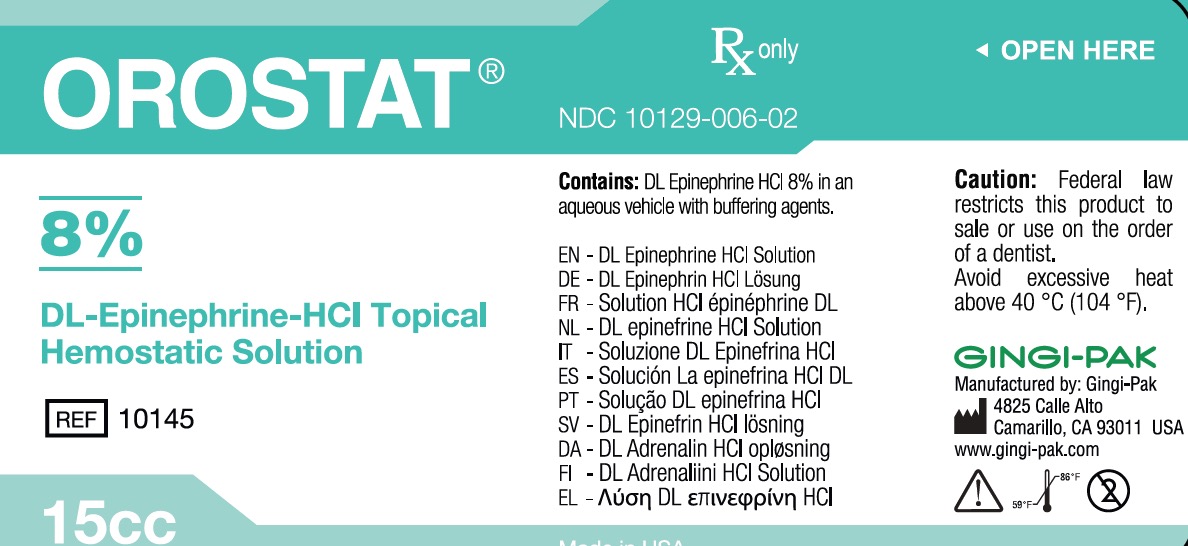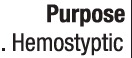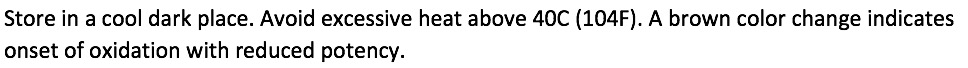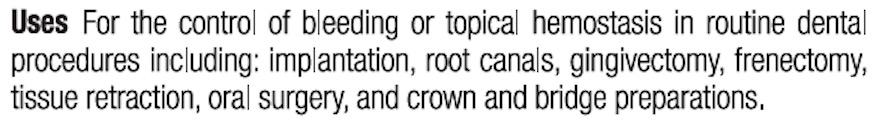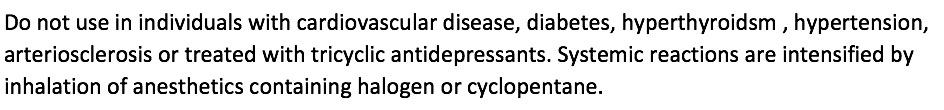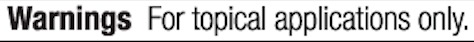 DRUG LABEL: Orostat 8%
NDC: 10129-006 | Form: SOLUTION
Manufacturer: Gingi-Pak a Division of the Belport
Category: otc | Type: HUMAN OTC DRUG LABEL
Date: 20180111

ACTIVE INGREDIENTS: EPINEPHRINE HYDROCHLORIDE 1200 mg/15 mL
INACTIVE INGREDIENTS: SODIUM DITHIONITE 37.5 mg/15 mL; SODIUM THIOSULFATE 15 mg/15 mL; SODIUM PHOSPHATE, MONOBASIC, ANHYDROUS 37.5 mg/15 mL; SODIUM CHLORIDE 49.5 mg/15 mL; PROPYLPARABEN 4.95 mg/15 mL; BENZYL ALCOHOL 0.15 mL/15 mL; EDETIC ACID 1.995 mg/15 mL; METHYLPARABEN 10.05 mg/15 mL

Orostat Solution